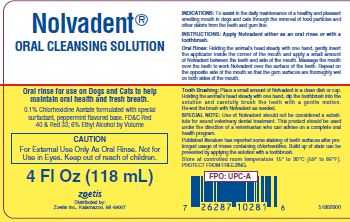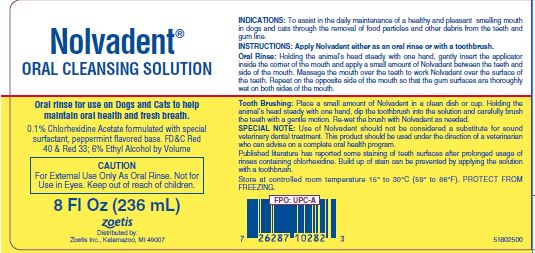 DRUG LABEL: Nolvadent Oral Cleansing
NDC: 54771-2800 | Form: SOLUTION
Manufacturer: Zoetis Inc.
Category: animal | Type: OTC ANIMAL DRUG LABEL
Date: 20240213

ACTIVE INGREDIENTS: CHLORHEXIDINE ACETATE 1 mg/1 mL

Nolvadent® Oral Cleansing Solution

DESCRIPTION

Nolvadent®
Oral Cleansing Solution
Oral rinse for use on Dogs and Cats to help maintain oral health and fresh breath.
0.1% Chlorhexidine Acetate formulated with special surfactant, peppermint flavored base. FD&C Red 40 & Red 33; 6% Ethyl Alcohol by Volume

CAUTION

For External Use Only As Oral Rinse. Not for Use in Eyes. Keep out of reach of children.

INDICATIONS

To assist in the daily maintenance of a healthy and pleasant smelling mouth in dogs and cats through the removal of food particles and other debris from the teeth and gum line.

INSTRUCTIONS

Apply Nolvadent either as an oral rinse or with a toothbrush.

Oral Rinse

Holding the animal's head steady with one hand, gently insert the applicator inside the corner of the mouth and apply a small amount of Nolvadent between the teeth and side of the mouth. Massage the mouth over the teeth to work Nolvadent over the surface of the teeth. Repeat on the opposite side of the mouth so that the gum surfaces are thoroughly wet on both sides of the mouth.

Tooth Brushing

Place a small amount of Nolvadent in a clean dish or cup. Holding the animal's head steady with one hand, dip the toothbrush into the solution and carefully brush the teeth with a gentle motion. Re-wet the brush with Nolvadent as needed.

SPECIAL NOTE

Use of Nolvadent should not be considered a substitute for sound veterinary dental treatment. This product should be used under the direction of a veterinarian who can advise on a complete oral health program.
Published literature has reported some staining of teeth surfaces after prolonged usage of rinses containing chlorhexidine. Build up of stain can be prevented by applying the solution with a toothbrush.

STORAGE AND HANDLING

Store at controlled room temperature 15° to 30°C (59° to 86°F).
PROTECT FROM FREEZING.

4 Fl Oz (118 mL)

8 Fl Oz (236 mL)
zoetis
Distributed by:
Zoetis Inc., Kalamazoo, MI 49007
1NOV400
8NOV400 09/13
14052800

1NOV401
8NOV401 09/13
14053200

PRINCIPAL DISPLAY PANEL - 4 Fl Oz (118 mL)

51802600

PRINCIPAL DISPLAY PANEL - 8 Fl Oz (236 mL)

51802500